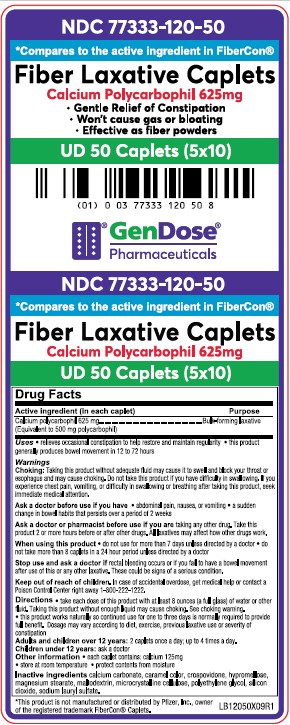 DRUG LABEL: FIBER LAXATIVE CAPLETS
NDC: 77333-120 | Form: TABLET
Manufacturer: Gendose Pharmaceuticals, LLC
Category: otc | Type: HUMAN OTC DRUG LABEL
Date: 20240108

ACTIVE INGREDIENTS: CALCIUM POLYCARBOPHIL 625 mg/1 1
INACTIVE INGREDIENTS: HYPROMELLOSE, UNSPECIFIED; POLYETHYLENE GLYCOL, UNSPECIFIED; SODIUM LAURYL SULFATE; SILICON DIOXIDE; CALCIUM CARBONATE; MAGNESIUM STEARATE; MALTODEXTRIN; CROSPOVIDONE; MICROCRYSTALLINE CELLULOSE; CARAMEL

GENDOSE - FIBER LAXATIVE CAPLETS (77333-120)

ACTIVE INGREDIENT (IN EACH CAPLET)

CALCIUM POLYCARBOPHIL 625 MG

(EQUIVALENT TO 500 MG POLYCARBOPHIL)

PURPOSE

BULK-FORMING LAXATIVE

USES

- RELIEVES OCCASIONAL CONSTIPATION TO HELP RESTORE AND MAINTAIN REGULARITY
- THIS PRODUCT GENERALLY PRODUCES BOWEL MOVEMENT IN 12 TO 72 HOURS

WARNINGS

CHOKING: TAKING THIS PRODUCT WITHOUT ADEQUATE FLUID MAY CAUSE IT TO SWELL AND BLOCK YOUR THROAT OR ESAPHAGUS AND MAY CAUSE CHOKING. DO NOT TAKE THIS PRODUCT IF YOU HAVE DIFFICULATY IN SWALLOWING. IF YOU EXPERIENCE CHEST PAIN, VOMITING, OR DIFFICULTY IN SWALLOWING OR BREATHING AFTER TAKING THIS PRODUCT, SEEK IMMEDIATE MEDICAL ATTENTION.

ASK A DOCTOR BEFORE USE IF YOU HAVE

- ADBOMINAL PAIN, NAUSEA, OR VOMITING
- A SUDDEN CHANGE IN BOWEL HABITS THAT PERSIST OVER A PERIOD OF 2 WEEKS

ASK A DOCTOR OR PHARMACIST BEFORE USE IF YOU ARE TAKING ANY OTHER DRUG. TAKE THIS PRODUCT 2 OR MORE HOURS BEFORE OR AFTER OTHER DRUGS. ALL LAXATIVES MAY AFFECT HOW DRUGS WORK.

WHEN USING THIS PRODUCT

- DO NOT USE FOR MORE THAN 7 DAYS UNLESS DIRECTED BY A DOCTOR
- DO NOT TAKE MORE THAN 8 CAPLETS IN A 24 HOUR PERIOD UNLESS DIRECTED BY A DOCTOR.

STOP USE AND ASK A DOCTOR IF RECTAL BLEEDING OCCURS OR IF YOU FAIL TO HAVE A BOWEL MOVEMENT AFTER USE OF THIS OR ANY OTHER LAXATIVES. THESE COULD BE SIGNS OF A SERIOUS CONDITION.

KEEP OUT OF REACH OF CHILDREN. IN CASE OF OVERDOSE, GET MEDICAL HELP OR CONTACT A POISON CONTROL CENTER RIGHT AWAY 1-800-222-1222.

DIRECTIONS

- TAKE EACH DOSE WITH AT LEAST 8 OUNCES (A FULL GLASS) OF WATER OR OTHER FLUID. TAKING THIS PRODUCT WITHOUT ENOUGH LIQUID MAY CAUSE CHOKING. SEE CHOKING WARNING.
- THIS PRODUCT WORKS NATURALLY SO CONTINUED USE FOR ONE TO THREE DAYS IS NORMALLY REQUIRED TO PROVIDE FULL BENEFIT. DOSAGE MAY VARY ACCORDING TO DIET, EXERCISE, PREVIOUS LAXATIVE USE OR SEVERITY OF CONSTIPATION

ADULTS AND CHILDREN OVER 12 YEARS: 2 CAPLETS ONCE A DAY; UP TO 4 TIMES A DAY.

CHILDREN UNDER 12 YEARS: ASK A DOCTOR

OTHER INFORMATION

- EACH CAPLET CONTAINS: CALCIUM 125MG
- STORE AT ROOM TEMPERATURE
- PROTECT CONTENTS FROM MOISTURE

INACTIVE INGREDIENTS

CALCIUM CARBONATE, CARAMEL COLOR, CROSPOVIDONE, HYPROMELLOSE, MAGNESIUM STEARATE, MALTODEXTRIN, MICROCRYSTALLINE CELLULOSE, POLYETHYLENE GLYCOL, SILICON DIOXIDE, SODIUM LAURYL SULFATE